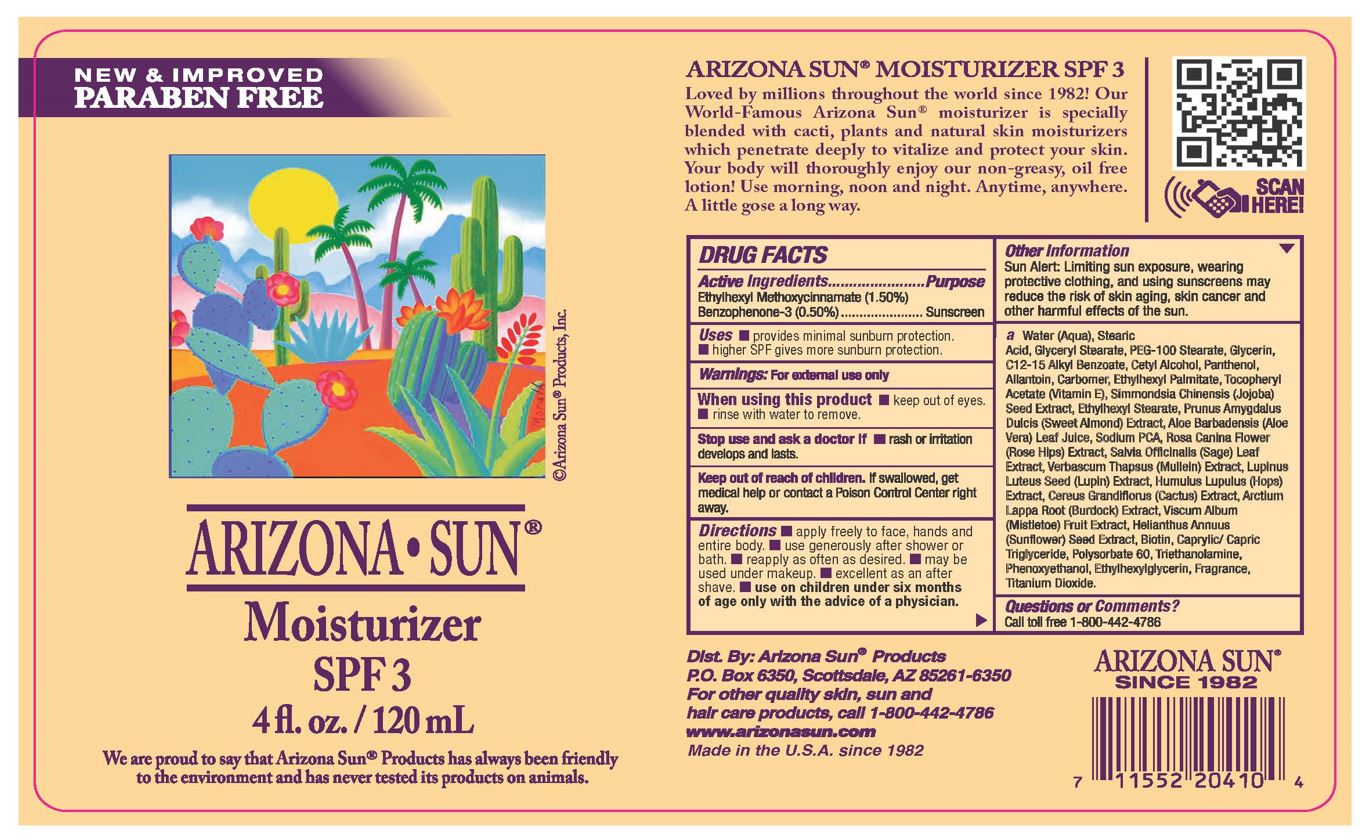 DRUG LABEL: Arizona Sun Moisturizer SPF 3
NDC: 61973-107 | Form: LOTION
Manufacturer: Arizona Sun Products
Category: otc | Type: HUMAN OTC DRUG LABEL
Date: 20240216

ACTIVE INGREDIENTS: OCTINOXATE 15 mg/1 g; OXYBENZONE 5 mg/1 g
INACTIVE INGREDIENTS: POLYSORBATE 60; ALKYL (C12-15) BENZOATE; SODIUM PYRROLIDONE CARBOXYLATE; BIOTIN; CETYL ALCOHOL; ALLANTOIN; .ALPHA.-TOCOPHEROL ACETATE; ROSA CANINA FLOWER; VISCUM ALBUM FRUIT; STEARIC ACID; HOPS; PHENOXYETHANOL; WATER; SAGE; MULLEIN LEAF; TROLAMINE; ETHYLHEXYLGLYCERIN; TITANIUM DIOXIDE; PEG-100 STEARATE; ALMOND OIL; ALOE VERA LEAF; GLYCERYL STEARATE SE; ETHYLHEXYL STEARATE; GLYCERIN; PANTHENOL; ETHYLHEXYL PALMITATE; SIMMONDSIA CHINENSIS SEED; ARCTIUM LAPPA ROOT; SUNFLOWER SEED; CARBOMER HOMOPOLYMER, UNSPECIFIED TYPE; LUPINUS LUTEUS SEED; SELENICEREUS GRANDIFLORUS FLOWER; CAPRYLIC/CAPRIC/LAURIC TRIGLYCERIDE

4 oz Moisturizer

Active Ingredients

Ethylhexyl Methoxycinnamate (1.50%), Benzophenone-3 (0.50%)

Purpose

Sunscreen

Uses

Provides minimal sunburn protection. Higher SPF gives more sunburn protection

Warnings

For external use only.

When using this product

keep out of eyes. Rinse with water to remove.

Stop and ask a doctor if

rash or irritation develops and lasts.

Keep out of the reach of children.

If swallowed get medical help or contact a poison control center right away.

Directions

Apply liberally and evenly to the skin 30 minutes before and during sun exposure. Reapply as needed or after towel drying, perspiring, swimming, and vigorous activities.

Other Information

Sun Alert: Limiting sun exposure, wearing protective clothing, and using suscreen may reduce the risk of skin aging, skin cancer and other harmful effects of the sun.

Inactive Ingredients

Water, Stearic Acid, Glyceryl Stearate, PEG-100 Stearate, Glycerin, C12-15 Alkyl Benzoate, Cetyl Alcohol, Panthenol, Allantoin, Carbomer, Ethylhexyl Palmitate, Tocopheryl Acetate (Vitamin E), Simmondsia Chinensis (Jojoba) Seed Oil, Ethylhexyl Stearate, Prunus Amygdalus Dulcis (Sweet Almond) Oil, Aloe Barbadensis (Aloe Vera) Leaf Juice, Sodium PCA, Rosa Canina Flower (Rose Hips) Extract, Salvia Officinalis (Sage) Leaf Extract, Verbascum Thapsus (Mullein) Extract, Lupinus Luteus Seed (Lupin) Extract, Humulus Lupulus (Hops) Extract, Cereus Grandiflorus (Cactus) Extract, Arctium Lappa Root (Burdock) Extract, Viscum Album (Mistletoe) Fruit Extract, Helianthus Annuus (Sunflower) Seed Extract, Biotin, Caprylic/ Capric Triglyceride, Polysorbate 60, Triethanolamine, Phenoxyethanol, Ethylhexylglycerin, Fragrance, Titanium Dioxide.

Questions or Comments?

Call toll free 1-800-442-4786